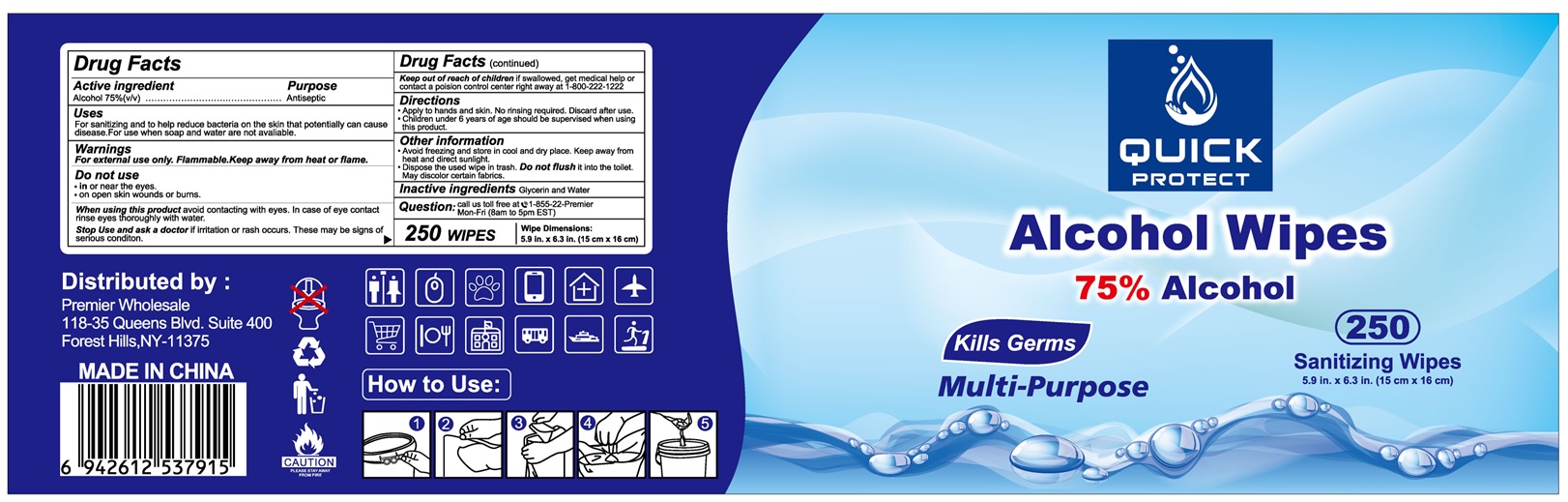 DRUG LABEL: Quick Protect
NDC: 80702-752 | Form: PATCH
Manufacturer: Reliance Enterprises USA Inc. DBA - Premier wholesale
Category: otc | Type: HUMAN OTC DRUG LABEL
Date: 20210118

ACTIVE INGREDIENTS: ALCOHOL 0.75 L/1 L
INACTIVE INGREDIENTS: GLYCERIN; WATER

Quick Protect Alcohol Wipes

Active Ingredient(s)

Alcohol 75%(v/v)

Purpose

Antiseptic

Uses

For sanitizng and to help reduce bacteria on skin that potentially can cause disease. For use when soap and water are not available.

Warnings

For external use only. Flammable. Keep away from heat or flame

Do not use

- in or near eyes
- on open skin wounds or burns

When using this product

Avoid contact with eyes. In case of contact with eyes, rinse eyes thoroughly with water.

Stop use and ask a doctor

If irritation or rash occurs. These may be signs of a serious condition.

Keep out of reach of children.

If swallowed, get medical help or contact a Poison Control Center right away at 1-800-222-1222

Directions

- Apply to hands and skin. No rinsing required. Discard after use.
- Children under 6 years of age should be supervised when using this product.

Other information

- Avoid freezing and store in cool and dry place. Keep away from heat and direct sunlight.
- Dispose of the wipes in trash. Do not flush it into the toilet. May discolor certain fabrics.

Inactive ingredients

Glycerin and Water

Question

Call us toll free at 1-855-22-Premier. Mon-Fri(8am to 5pm EST)

Principal Display Panel

NDC 80702-752-50

Quick PROTECT

Alcohol Wipes

75% Alcohol

Kills Germs

Multi-purpose

250 Sanitizing Wipes

5.9 in. X 6.3 in. (15 cm X 16 cm)